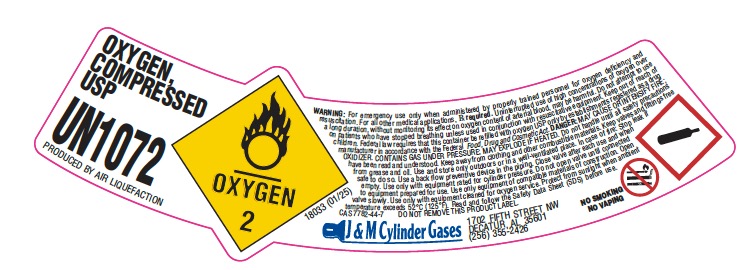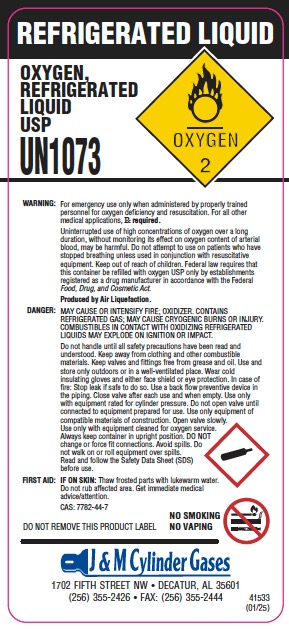 DRUG LABEL: Oxygen
NDC: 63862-004 | Form: GAS
Manufacturer: J & M CYLINDER GASES, INC.
Category: prescription | Type: HUMAN PRESCRIPTION DRUG LABEL
Date: 20251201

ACTIVE INGREDIENTS: OXYGEN 990 mL/1 L

oxygen

PACKAGE LABEL

OXYGEN COMPRESSED USP
UN1072
PRODUCED BY AIR LIQUEFACTION
WARNING: For emergency use only when administered by properly trained personnel for oxygen deficiency and resuscitation. For all other medical applications, Rx required. Uninterrupted use of high concentrations of oxygen over a long duration, without monitoring its effect on oxygen content of arterial blood, may be harmful. Do not attempt to use on patients who have stopped breathing unless used in conjunction with resuscitative equipment.
DANGER: MAY CAUSE OR INTENSIFY FIRE; OXIDIZER. CONTAINS GAS UNDER PRESSURE; MAY EXPLODE IF HEATED. Obtain, read and follow all safety instructions before use. Keep away from clothing and other combustible materials. Keep valves and fittings free from grease and oil. Use and store only outdoors or with adequate ventilation. Store in a well-ventilated place. In case of fire: Stop leak if safe to do so. Use a backflow preventive device in the piping. Use only equipment of compatible materials of construction and rated for cylinder pressure. Use only with equipment cleaned for oxygen service. Do not open valve until connected to equipment prepared for use. Open valve slowly. Close valve after each use and when empty. Protect from sunlight when ambient temperature exceeds 52C (125F). Read and follow the Safety Data Sheet (SDS) before use.
CAS: 7782-44-7
NO SMOKING
NO VAPING
DO NOT REMOVE THIS PRODUCT LABEL
J & M Cylinder Gases
1702 FIFTH STREET NW
DECATUR, AL 35601
(256) 355-2426

PACKAGE LABEL

REFRIGERATED LIQUID
OXYGEN, REFRIGERATED LIQUID USP
UN1073
WARNING: For emergency use only when administered by properly trained personnel for oxygen deficiency and resuscitation. For all other medical applications, Rx required.
Uninterrupted use of high concentrations of oxygen over a long duration, without monitoring its effect on oxygen content of arterial blood, may be harmful. Do not attempt to use on patients who have stopped breathing unless used in conjunction with resuscitative equipment.
Federal law requires that this container be refilled with oxygen USP only by establishments registered as a drug manufacturer in accordance with the Federal Food, Drug, and Cosmetic Act.
Produced by Air Liquefaction.
DANGER: MAY CAUSE OR INTENSIFY FIRE; OXIDIZER. CONTAINS REFRIGERATED GAS; MAY CAUSE CRYOGENIC BURNS OR INJURY. COMBUSTIBLES IN CONTACT WITH OXIDIZING REFRIGERATED LIQUIDS MAY EXPLODE ON IGNITION OR IMPACT.
Obtain, read and follow all safety instructions before use. Keep away from clothing and other combustible materials. Keep valves and fittings free from grease and oil. Use and store only outdoors or in a well-ventilated place. Wear cold insulating gloves/face shield/eye protection. In case of fire: Stop leak if safe to do so. Store locked up. Dispose of contents/container in accordance with local/regional/national/international regulations. Use a backflow preventive device in the piping. Use only equipment of compatible materials of construction and rated for cylinder pressure. Use only with equipment cleaned for oxygen service. Do not change or force fit connections. Close valve after each use and when empty. Always keep container in upright position. Avoid spills. Do not walk on or roll equipment over spills. Read and follow the Safety Data Sheet (SDS) before use.
FIRST AID: IF ON SKIN: Thaw frosted parts with lukewarm water. Do not rub affected area. Get immediate medical advice/attention.
CAS: 7782-44-7
NO SMOKING
NO VAPING
DO NOT REMOVE THIS PRODUCT LABEL
J & M Cylinder Gases
1702 FIFTH STREET NW • DECATUR, AL 35601
(256) 355-2426 • FAX: (256) 355-2444